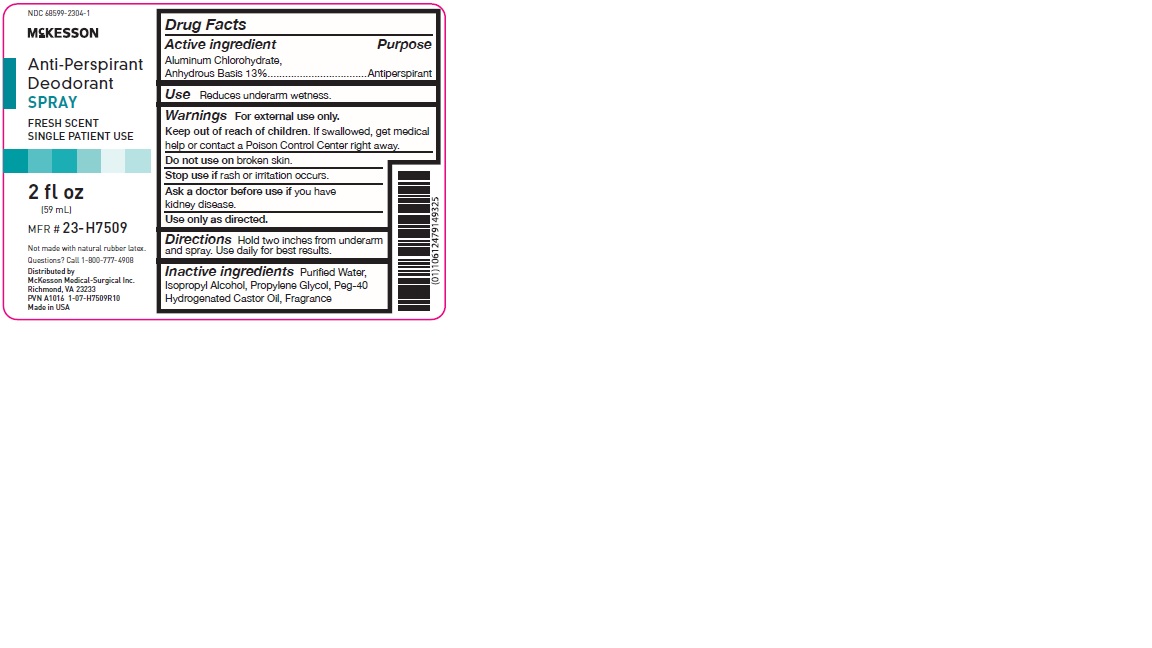 DRUG LABEL: Anti-Perspirant Deodorant
NDC: 68599-2304 | Form: SPRAY
Manufacturer: McKesson Medical-Surgical Inc.
Category: otc | Type: HUMAN OTC DRUG LABEL
Date: 20260112

ACTIVE INGREDIENTS: ALUMINUM CHLOROHYDRATE 130 mg/1 mL
INACTIVE INGREDIENTS: WATER; ISOPROPYL ALCOHOL; PROPYLENE GLYCOL; POLYOXYL 40 HYDROGENATED CASTOR OIL

Anti-Perspirant Deodorant Spray

Drug Facts

Active ingredient

Aluminum Chlorohydrate, Anhydrous Basis 13%

Purpose

Antiperspirant

Use

Reduces underarm wetness.

Warnings

FOR EXTERNAL USE ONLY.

KEEP OUT OF REACH OF CHILDREN.

Do not use on broken skin.

Stop use if rash or irritation occurs.

Ask a doctor before use if you have kidney disease. If swallowed, get medical help or contact a Poison Control Center immediately. Use only as directed.

Directions

Hold two inches from underarm and spray. Use daily for best results.

Inactive ingredients

Purified Water, Isopropyl Alcohol, Propylene Glycol, Peg-40 Hydrogenated Castor Oil, Fragrance

PRINCIPAL DISPLAY PANEL - 59 mL Bottle Label

McKESSON

Anti-Perspirant
Deodorant
Spray

Fresh Scent
•
Single Patient use

2 fl. oz. (59 ml)